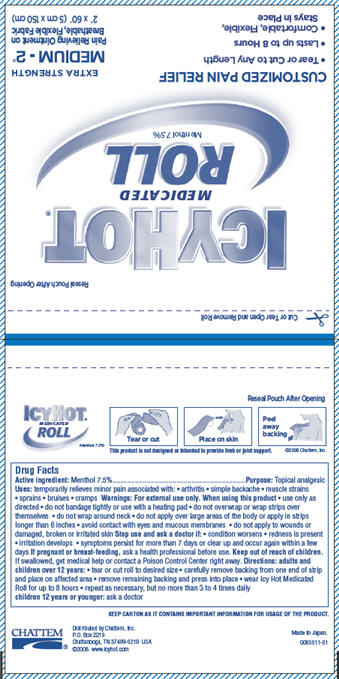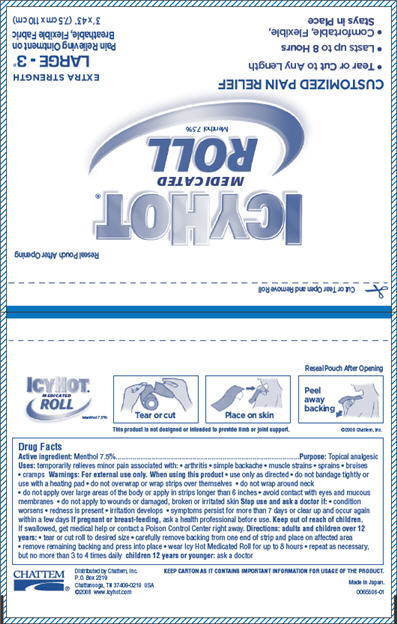 DRUG LABEL: Icy Hot
NDC: 44014-085 | Form: PATCH
Manufacturer: Nichiban Company Limited
Category: otc | Type: HUMAN OTC DRUG LABEL
Date: 20091223

ACTIVE INGREDIENTS: MENTHOL 787.5 mg/1 1

Drug Facts

Active ingredient

Menthol 7.5%

Purpose

Topical analgesic

Uses

temporarily relieves minor pain associated with:

- arthritis
- simple backache
- muscle strains
- sprains
- bruises
- cramps

Warnings:

For external use only

When using this product

- use only as directed
- do not bandage tightly or use with a heating pad
- do not overwrap or wrap strips over themselves
- do not wrap around neck
- do not apply over large areas of the body or apply in strips longer than 6 inches
- avoid contact with eyes and mucous membranes
- do not apply to wounds or damaged, broken or irritated skin

Stop use and ask a doctor if:

- condition worsens
- redness is present
- irritation develops
- symptoms persist for more than 7 days or clear up and occur again within a few days

If pregnant or breast-feeding,

ask a health professional before use.

Keep out of reach of children.

If swallowed, get medical help or contact a Poison Control Center right away.

Directions:

adults and children over 12 years:

- tear or cut roll to desired size
- carefully remove backing from one end of strip and place on affected area
- remove remaining backing and press into place
- wear Icy Hot Medicated Roll for up to 8 hours
- repeat as necessary, but no more than 3 to 4 times daily

children 12 years or younger: ask a doctor

Keep carton as it contains important information for usage of this product.

Distributed by Chattem, Inc.

P.O. Box 2219

Chattanooga, TN 37409-0219 USA

© 2009 www.icyhot.com

MADE IN JAPAN
[NDC Code]

Principal Display Panel - Medium Roll, Pouch

Reseal Pouch After Opening

ICY HOT® MEDICATED ROLL
Menthol 7.5%

CUSTOMIZED PAIN RELIEF

- Tear or Cut to Any Length
- Lasts up to 8 Hours
- Comfortable, Flexible, Stays in Place

EXTRA STRENGTH
MEDIUM - 2"

Pain Relieving Ointment on Breathable, Flexible Fabric

2" x 60" (5 cm x 150 cm)

Medium Roll Pouch

Principal Display Panel - Large Roll, Pouch

Reseal Pouch After Opening

ICY HOT® MEDICATED ROLL
Menthol 7.5%

CUSTOMIZED PAIN RELIEF

- Tear or Cut to Any Length
- Lasts up to 8 Hours
- Comfortable, Flexible, Stays in Place

EXTRA STRENGTH
LARGE - 3"

Pain Relieving Ointment on Breathable, Flexible Fabric

3" x 43" (7.5 cm x 110 cm)

Large Roll Pouch